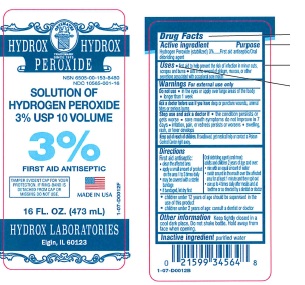 DRUG LABEL: Hydrogen Peroxide
NDC: 10565-001 | Form: SOLUTION
Manufacturer: Hydrox Laboratories
Category: otc | Type: HUMAN OTC DRUG LABEL
Date: 20260112

ACTIVE INGREDIENTS: HYDROGEN PEROXIDE 3 mL/100 mL
INACTIVE INGREDIENTS: WATER

SOLUTION OF
HYDROGEN PEROXIDE
3% USP 10 VOLUME

Drug Facts

Active ingredient

Hydrogen Peroxide (stabilized) 3%

Purpose

First aid antiseptic/Oral debriding agent

Uses

- first aid to help prevent the risk of infection in minor cuts, scrapes and burns
- aids in the removal of phlegm, mucous, or other secretions associated with occasional sore mouth

Warnings

WHEN USING

For external use only

Do not use

- in the eyes or apply over large areas of the body
- longer than 1 week

Ask a doctor before use if you havedeep or puncture wounds, animal bites or serious burns

Stop use and ask a doctor if

- the condition persists or gets worse
- sore mouth symptoms do not improve in 7 days
- irritation, pain, or redness persists or worsens
- swelling, rash, or fever develops

Keep out of reach of children.If swallowed, get medical help or contact a Poison Control Center right away.

Directions

First aid antiseptic:

- clean the affected area
- apply a small amount of product on the area 1 to 3 times daily
- may be covered with a sterile bandage
- if bandaged, let dry first

Oral debriding agent (oral rinse):
adults and children 2 years of age and over:

- mix with an equal amount of water
- swish around in the mouth over the affected area for at least 1 minute and then spit out
- use up to 4 times daily after meals and at bedtime or as directed by a dentist or doctor

- children under 12 years of age should be supervised in the use of this product
- children under 2 years of age: consult a dentist or doctor

Other information

Keep tightly closed in a cool dark place. Do not shake bottle. Hold away from face when opening.

Inactive ingredient

Purified Water

PRINCIPAL DISPLAY PANEL - 473 mL Bottle Label

OPTIMATES
HYDROX
CHEMICALS
TRADEMARK
SINCE 1913

Hydrox

NDC 10565-001-16

SOLUTION OF
HYDROGEN PEROXIDE
3% USP 10 VOLUME

3%

TAMPER EVIDENT CAP FOR YOUR PROTECTION.

IF RING-BAND IS DETACHED FROM CAP OR MISSING DO NOT USE.

FIRST AID ANTISEPTIC
Made in USA

16 FL. OZ. (473 mL)